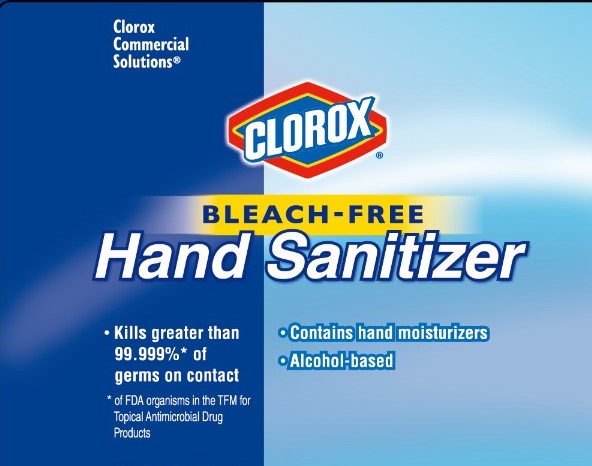 DRUG LABEL: Clorox Hand Sanitizer
NDC: 69540-0028 | Form: SOLUTION
Manufacturer: Brand Buzz LLC
Category: otc | Type: HUMAN OTC DRUG LABEL
Date: 20230202

ACTIVE INGREDIENTS: ALCOHOL 71 mL/100 mL
INACTIVE INGREDIENTS: WATER; GLYCERYL LAURATE; GLYCERIN; ISOPROPYL ALCOHOL

Clorox Hand Sanitizer (Bleach-Free)

Active Ingredient

Alcohol 71% v/v

Purpose

Antiseptic

Use

Hand sanitizer to help decrease bacteria on skin that can potentially cause disease.

Warnings

Flammable. Keep away from fire or flame.

For external use only.

Do not use in the eyes.

Stop use and ask a doctor if

- irritation and redness develop
- condition persists for more than 72 hours

Keep out of reach of children. If swallowed, get medical help or contact a poison control center immediately.

Directions

- Spray on clean, dry hands and nails
- Wet hands thoroughly with product
- Rub hands together for no less than 15 seconds, paying particular attention to interdigital spaces, fingernails and cuticles
- Allow to dry without wiping
- Rub hands together briskly until dry

Other Information

- Store in a cool, dry place below 104 deg F (40 C)

Inactive Ingredients

Water, Isopropyl Alcohol, Glycerin, Glyceryl Laurate

Questions or Comments?

Viisit us at www.cloroxprofessional.com or call 1-888-508-4750.

Package Label: 59ml/500ml

Clorox Commercial Solutions®

CLOROX

BLEACH-FREE

Hand Sanitizer

Kills greater than 99.999%* of germs on contact

Contains hand moisturizers

Alcohol-based

*of FDA organism in the TFM for Topical Antimicrobial Drug Products